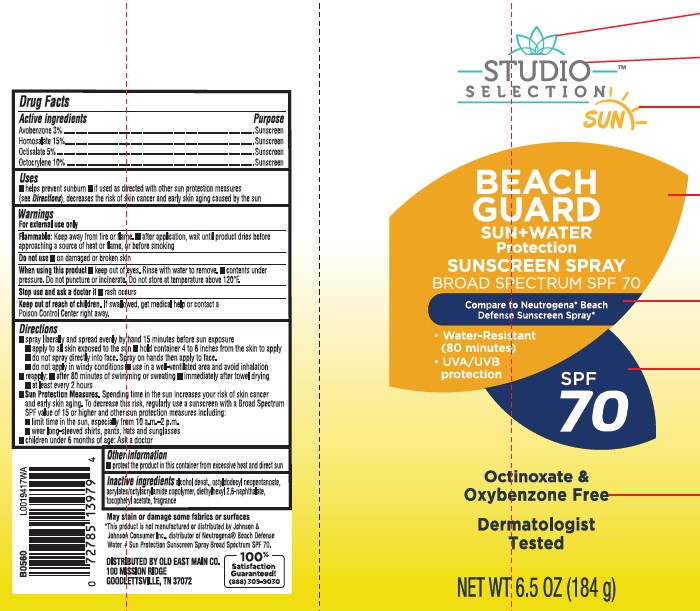 DRUG LABEL: sunscreen
NDC: 55910-983 | Form: SPRAY
Manufacturer: Old East Main CO.
Category: otc | Type: HUMAN OTC DRUG LABEL
Date: 20250402

ACTIVE INGREDIENTS: AVOBENZONE 30 mg/1 g; HOMOSALATE 150 mg/1 g; OCTISALATE 50 mg/1 g; OCTOCRYLENE 100 mg/1 g
INACTIVE INGREDIENTS: ALCOHOL; OCTYLDODECYL NEOPENTANOATE; BUTYL ACRYLATE/METHYL METHACRYLATE/METHACRYLIC ACID COPOLYMER (18000 MW); DIETHYLHEXYL 2,6-NAPHTHALATE; .ALPHA.-TOCOPHEROL ACETATE

Studio Selection 983.000/983AA
Beach Guard Sunscreen Spray SPF 70

Active ingredients

Avobenzone 3%

Homosalate 15%

Octisalate 5%

Octocrylene 10%

purpose

sunscreen

uses

- helps prevent sunburn
- if used as directed with other sun protection measures (see Directions), decreases the risk of skin cancer and early skin aging caused by the sun

warnings

For external use only

Flammable

Keep away from fire or flame.

- after application, wait until product dries before approaching a source of heat or flame, or before smoking

do not use

- on damaged or broken skin

When using this product

- keep out of eyes. Rinse with water to remove.
- contents under pressure. Do not puncture or incinerate. Do not store at temperature above 120ºF.

stop use and ask a doctor if

- rash occurs

Keep out of reach of children.

If swallowed, get medical help or contact a Poison Conrol Center right away.

Directions

■ spray liberally and spread evenly by hand 15 minutes before sun exposure
■ apply to all skin exposed to the sun
■ hold container 4 to 6 inches from the skin to apply
■ do not spray directly into face. Spray on hands then apply to face.
■ do not apply in windy conditions
■ use in a well-ventilated area and avoid inhalation
■ reapply:
■ after 80 minutes of swimming or sweating
■ immediately after towel drying
■ at least every 2 hours
■ Sun Protection Measures. Spending time in the sun increases your risk of skin cancer and early skin aging. To decrease this risk, regularly use a sunscreen with a Broad Spectrum SPF value of 15 or higher and other sun protection measures including:
■ limit time in the sun, especially from 10 a.m.–2 p.m.
■ wear long-sleeved shirts, pants, hats and sunglasses
■ children under 6 months of age: Ask a doctor

other information

- protect the product in the container from excessive heat and direct sun

inactive ingredients

alcohol denat., octyldodecyl neopentanoate, acrylates/octylacrylamide copolymer, diethylhexyl 2,6-naphthalate, tocopheryl acetate, fragrance

Disclaimer

May stain or damage some fabrics of surfaces

*This product is not manufactured or distributed by Johnson & Johnson Consumer Inc., distributor of NeutrogenaBeach Defense Water + Sun Protection Sunscreen Spray Broad Spectrum SPF 70.

ADVERSE REACTION

DISTRIBUTED BY OLD EAST MAIN CO.

100 MISSION RIDGE

GOODLETTSVILLE, TN 37072

100% Satisfaction Guaranteed!

(888) 309-9030

principal display panel

STUDIO SELECTION™

SUN

BEACH GUARD

SUN + WATER

Protection

SUNSCREEN SPRAY

BROAD SPECTRUM SPF 70

Compare to Neutrogena®Beach Defense Sunscreen Spray

- Water-Resistant (80 minutes)
- UVA/UVB protection

SPF 70

Octinoxate & Oxybenzone Free

Dermatologist Tested

NET WT 6.5 OZ (184 g)